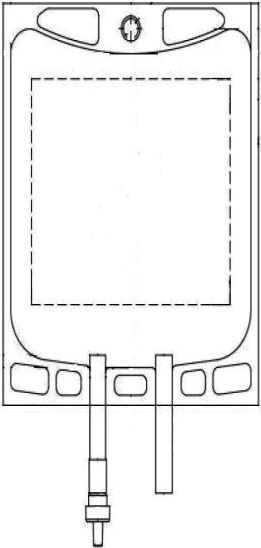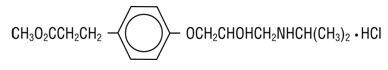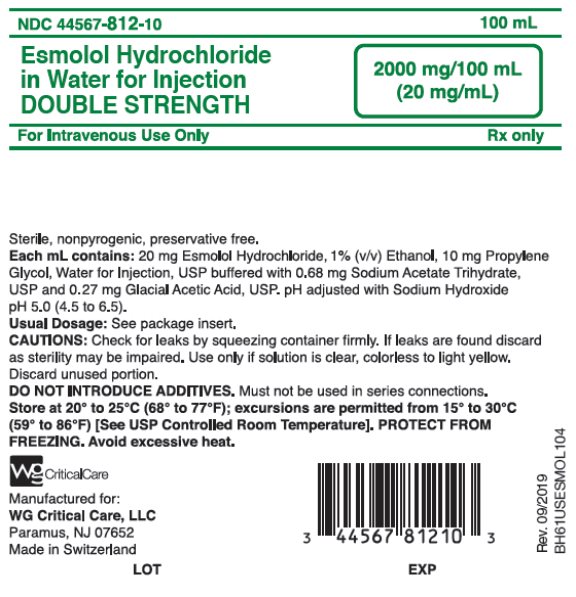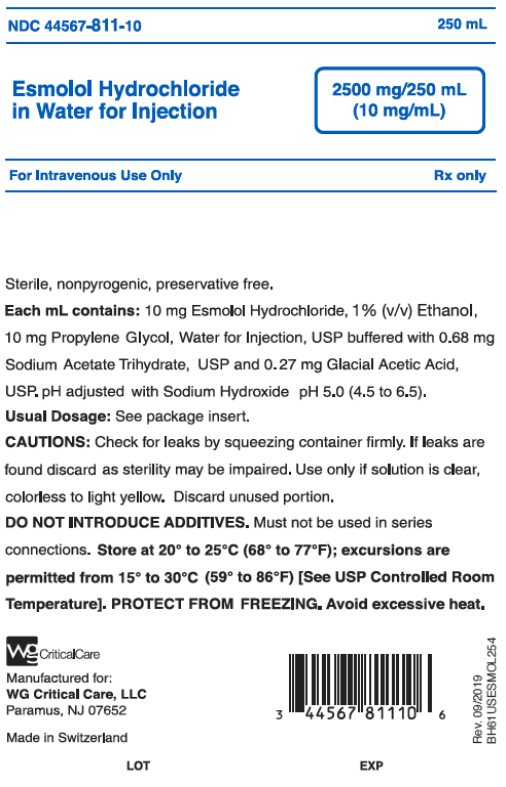 DRUG LABEL: Esmolol Hydrochloride in Water
NDC: 44567-811 | Form: INJECTION
Manufacturer: WG Critical Care, LLC
Category: prescription | Type: HUMAN PRESCRIPTION DRUG LABEL
Date: 20240531

ACTIVE INGREDIENTS: ESMOLOL HYDROCHLORIDE 10 mg/1 mL

HIGHLIGHTS OF PRESCRIBING INFORMATION

These highlights do not include all the information needed to use ESMOLOL HYDROCHLORIDE IN WATER FOR INJECTION safely and effectively. See full prescribing information for ESMOLOL HYDROCHLORIDE IN WATER FOR INJECTION.
ESMOLOL HYDROCHLORIDE IN WATER FOR INJECTION, for intravenous use
Initial U.S. Approval: 1986

1 INDICATIONS AND USAGE

Esmolol Hydrochloride is a beta-adrenergic blocker indicated for the short-term treatment of:

1. Control of ventricular rate in supraventricular tachycardia including atrial fibrillation and atrial flutter and control of heart rate in noncompensatory sinus tachycardia (1.1)
2. Control of perioperative tachycardia and hypertension (1.2)

2 DOSAGE AND ADMINISTRATION

1. Administer intravenously (2.1, 2.2)
2. Titrate using ventricular rate or blood pressure at ≥ 4-minute intervals (2.1, 2.2)
3. Supraventricular tachycardia (SVT) or noncompensatory sinus tachycardia (2.1)
  Optional loading dose: 500 mcg/kg infused over one minute
  Then 50 mcg/kg/min for the next 4 minutes
  Titrate as needed to a maximum of 200 mcg/kg/min
  Additional loading doses may be administered
4. Perioperative tachycardia and hypertension (2.2)
  Loading dose: 500 mcg/kg over 1 minute for gradual control (1 mg/kg over 30 seconds for immediate control)
  Then 50 mcg/kg/min for gradual control (150 mcg/kg/min for immediate control) adjusted to a maximum of 200 (tachycardia) or 300 (hypertension) mcg/kg/min

3 DOSAGE FORMS AND STRENGTHS

1. Injection: 2500 mg/250 mL (10 mg/mL) in 250 mL Premixed Injection bag (3)
2. Injection: 2000 mg/100 mL (20 mg/mL) in 100 mL DOUBLE STRENGTH Premixed Injection bag (3)

4 CONTRAINDICATIONS

1. Severe sinus bradycardia (4)
2. Heart block greater than first degree (4)
3. Sick sinus syndrome (4)
4. Decompensated heart failure (4)
5. Cardiogenic shock (4)
6. Coadministration of IV cardiodepressant calcium-channel antagonists (e.g. verapamil) in close proximity to esmolol (4, 7)
7. Pulmonary hypertension (4)
8. Known hypersensitivity to esmolol (4)

5 WARNINGS AND PRECAUTIONS

1. Risk of hypotension, bradycardia, and cardiac failure: Monitor for signs and symptoms of cardiovascular adverse effects. Reduce dose or discontinue use (5.1, 5.2, 5.3, 5.8)
2. Risk of exacerbating reactive airway disease (5.4)
3. Diabetes mellitus: May mask symptoms of hypoglycemia and alter glucose levels; monitor (5.5)
4. Risk of unopposed alpha-agonism and severe hypertension in untreated pheochromocytoma (5.7)
5. Risk of myocardial ischemia when abruptly discontinued in patients with coronary artery disease (5.10, 5.11)

6 ADVERSE REACTIONS

1. Most common adverse reactions (incidence> 10%) are symptomatic hypotension (hyperhidrosis, dizziness) and asymptomatic hypotension (6)

To report SUSPECTED ADVERSE REACTIONS, contact WG Critical Care, LLC at 1-866-562-4708 or FDA at 1-800-FDA-1088 or www.fda.gov/medwatch.

7 DRUG INTERACTIONS

1. Digitalis glycosides: Risk of bradycardia (7)
2. Anticholinesterases: Prolongs neuromuscular blockade (7)
3. Antihypertensive agents: Risk of rebound hypertension (7)
4. Sympathomimetic drugs: Dose adjustment needed (7)
5. Vasoconstrictive and positive inotropic effect substances: Avoid concomitant use (7)

FULL PRESCRIBING INFORMATION

1 INDICATIONS AND USAGE

1.1 Supraventricular Tachycardia or Noncompensatory Sinus Tachycardia

Esmolol hydrochloride is indicated for the rapid control of ventricular rate in patients with atrial fibrillation or atrial flutter in perioperative, postoperative, or other emergent circumstances where short term control of ventricular rate is desirable.

Esmolol hydrochloride is also indicated in noncompensatory sinus tachycardia where, in the physician’s judgment, the rapid heart rate requires specific intervention. Esmolol hydrochloride is intended for short-term use.

1.2 Intraoperative and Postoperative Tachycardia and Hypertension

Esmolol hydrochloride is indicated for the short-term treatment of tachycardia and hypertension that occur during induction and tracheal intubation, during surgery, on emergence from anesthesia and in the postoperative period, when in the physician’s judgment such specific intervention is considered indicated.

Use of esmolol hydrochloride to prevent such events is not recommended.

2 DOSAGE AND ADMINISTRATION

2.1 Dosing for the Treatment of Supraventricular Tachycardia or Noncompensatory Sinus Tachycardia

Esmolol hydrochloride is administered by continuous intravenous infusion with or without a loading dose. Additional loading doses and/or titration of the maintenance infusion (stepwise dosing) may be necessary based on desired ventricular response.

Table 1. Step-Wise Dosing

Step | Action
1 | Optional loading dose (500 mcg/kg over 1 minute), then 50 mcg/kg/min for 4 min
2 | Optional loading dose if necessary, then 100 mcg/kg/min for 4 min
3 | Optional loading dose if necessary, then 150 mcg/kg/min for 4 min
4 | If necessary increase dose to 200 mcg/kg/min

In the absence of loading doses, continuous infusion of a single concentration of esmolol reaches pharmacokinetic and pharmacodynamic steady-state in about 30 minutes.

The effective maintenance dose for continuous and step-wise dosing is 50 to 200 mcg/kg/min, although doses as low as 25 mcg/kg/min have been adequate. Dosages greater than 200 mcg/kg/min provide little added heart-rate lowering effect, and the rate of adverse reactions increases.

Maintenance infusions may be continued for up to 48 hours.

2.2 Intraoperative and Postoperative Tachycardia and Hypertension

In this setting it is not always advisable to slowly titrate to a therapeutic effect. Therefore, two dosing options are presented: immediate control and gradual control.

Immediate Control

1. Administer 1 mg/kg as a bolus dose over 30 seconds followed by an infusion of 150 mcg/kg/min if necessary.
2. Adjust the infusion rate as required to maintain desired heart rate and blood pressure. Refer to Maximum Recommended Doses below.

Gradual Control

1. Administer 500 mcg/kg as a bolus dose over 1 minute followed by a maintenance infusion of 50 mcg/kg/min for 4 minutes.
2. Depending on the response obtained, continue dosing as outlined for supraventricular tachycardia (refer to Figure 1). Refer to Maximum Recommended Doses below.

Maximum Recommended Doses

1. For the treatment of tachycardia, maintenance infusion dosages greater than 200 mcg/kg/min are not recommended; dosages greater than 200 mcg/kg/min provide little additional heart rate-lowering effect, and the rate of adverse reactions increases.
2. For the treatment of hypertension, higher maintenance infusion dosages (250 to 300 mcg/kg/min) may be required. The safety of doses above 300 mcg/kg/min has not been studied.

2.3 Transition from Esmolol Hydrochloride Injection Therapy to Alternative Drugs

After patients achieve adequate control of the heart rate and a stable clinical status, transition to alternative antiarrhythmic drugs may be accomplished.

When transitioning from esmolol hydrochloride to alternative drugs, consider the labeling instructions of the alternative drug selected and reduce the dosage of esmolol hydrochloride as follows:

1. Thirty minutes following the first dose of the alternative drug, reduce the esmolol hydrochloride infusion rate by one-half (50%).
2. After administration of the second dose of the alternative drug, monitor the patient's response, and, if satisfactory control is maintained for the first hour, discontinue the esmolol hydrochloride infusion.

2.4 Directions for Use

Avoid infusions into small veins or through butterfly catheters because of the risk of extravasation [see Adverse Reactions (6.1)].

Each bag is for single patient use only and does not contain any preservatives. Once drug has been withdrawn from ready-to-use bag, the infusion of the bag contents should commence immediately and complete within 24 hours. Discard any unused.

Do not remove unit from overwrap until ready to use. Do not use if overwrap has been previously opened or damaged. The overwrap is a moisture barrier. The inner bag maintains sterility of the solution. Tear overwrap at notch and remove premixed bag.

Check for minute leaks by squeezing the inner bag firmly. If leaks are found, discard solution, as sterility may be impaired. Do not use unless the solution is clear (colorless to light yellow) and the seal is intact.

Preparation for intravenous administration:

- Use aseptic technique.
- Suspend premixed bag from eyelet support.
- Remove plastic protector from delivery port at bottom of bag.
- Attach administration set.
- Refer to complete directions accompanying set.

Do not use plastic containers in series connections. Such use could result in an embolism due to residual air being drawn from the primary container before administration of the fluid from the secondary container is completed.

Esmolol Hydrochloride is not compatible with Sodium Bicarbonate (5%) solution (limited stability) or furosemide (precipitation).

Parenteral drug products should be inspected visually for particulate matter and discoloration prior to administration, whenever solution and container permit.

Premixed Bag

1. The medication port is to be used solely for withdrawing an initial bolus from the bag.
2. Use aseptic technique when withdrawing the bolus dose.
3. Do not add any additional medications to the bag.

Figure 1. Dual Port Bag

3 DOSAGE FORMS AND STRENGTHS

Table 2. Esmolol Hydrochloride in Water for Injection Presentations
Presentations; Product Name | Esmolol Hydrochloride | Esmolol Hydrochloride DOUBLE STRENGTH
Total Dose | 2500 mg/250 mL | 2000 mg/100 mL
Esmolol Hydrochloride Concentration | 10 mg/mL | 20 mg/mL
Packaging | 250 mL Bag | 100 mL Bag

4 CONTRAINDICATIONS

Esmolol hydrochloride is contraindicated in patients with:

1. Severe sinus bradycardia, heart block greater than first degree, sick sinus syndrome: May precipitate or worsen bradycardia resulting in cardiogenic shock and cardiac arrest [see Warnings and Precautions (5.2)].
2. Decompensated heart failure: May worsen heart failure and cause cardiogenic shock
3. Concomitant use of IV cardiodepressant calcium-channel antagonists (e.g., verapamil): May cause cardiovascular collapse.
4. Hypersensitivity reactions, including anaphylaxis, to esmolol or any of the inactive ingredients of the product (cross-sensitivity between beta-blockers is possible).

5 WARNINGS AND PRECAUTIONS

5.1 Hypotension

Hypotension can occur at any dose but is dose-related. Patients with hemodynamic compromise or on interacting medications are at particular risk. Severe reactions may include loss of consciousness, cardiac arrest, and death. For control of ventricular heart rate, maintenance doses greater than 200 mcg/kg/min are not recommended. Monitor patients closely, especially if pretreatment blood pressure is low. In case of an unacceptable drop in blood pressure, reduce or stop esmolol hydrochloride. Reduction of dose or termination of infusion reverses hypotension, usually within 30 minutes.

5.2 Bradycardia

Bradycardia, including sinus pause, heart block, severe bradycardia, and cardiac arrest have occurred with the use of esmolol hydrochloride. Patients with first-degree atrioventricular block, sinus node dysfunction, or conduction disorders may be at increased risk. Monitor heart rate and rhythm in patients receiving esmolol hydrochloride [see Contraindications (4)].

If severe bradycardia develops, reduce or stop esmolol hydrochloride.

5.3 Cardiac Failure

Beta-blockers, like esmolol hydrochloride, can cause depression of myocardial contractility and may precipitate heart failure and cardiogenic shock. If the patient develops signs or symptoms of cardiac failure, stop esmolol hydrochloride and start supportive therapy.

5.4 Reactive Airways Disease

Patients with reactive airways disease should, in general, not receive beta-blockers. Because of its relative beta1 selectivity and titratability, titrate esmolol to the lowest possible effective dose. In the event of bronchospasm, stop the infusion immediately; a beta2 stimulating agent may be administered with appropriate monitoring of ventricular rate.

5.5 Hypoglycemia

Beta-blockers may prevent early warning signs of hypoglycemia, such as tachycardia, and increase the risk for severe or prolonged hypoglycemia at any time during treatment, especially in patients with diabetes mellitus or children and patients who are fasting (i.e., surgery, not eating regularly, or are vomiting). If severe hypoglycemia occurs, patients should be instructed to seek emergency treatment.

5.6 Use in Patients with Prinzmetal’s Angina

Beta-blockers may exacerbate anginal attacks in patients with Prinzmetal’s angina because of unopposed alpha receptor–mediated coronary artery vasoconstriction. Do not use nonselective beta-blockers.

5.7 Use in Patients with Pheochromocytoma

If esmolol hydrochloride is used in the setting of pheochromocytoma, give it in combination with an alpha-blocker, and only after the alpha-blocker has been initiated. Administration of beta-blockers alone in the setting of pheochromocytoma has been associated with a paradoxical increase in blood pressure from the attenuation of beta-mediated vasodilation in skeletal muscle.

5.8 Use in Hypovolemic Patients

In hypovolemic patients, esmolol hydrochloride can attenuate reflex tachycardia and increase the risk of hypotension.

5.9 Use in Patients with Peripheral Circulatory Disorders

In patients with peripheral circulatory disorders (including Raynaud’s disease or syndrome, and peripheral occlusive vascular disease), esmolol hydrochloride may aggravate peripheral circulatory disorders.

5.10 Abrupt Discontinuation of Esmolol Hydrochloride

Severe exacerbations of angina, myocardial infarction, and ventricular arrhythmias have been reported in patients with coronary artery disease upon abrupt discontinuation of beta-blocker therapy. Observe patients for signs of myocardial ischemia when discontinuing esmolol hydrochloride.

Heart rate increases moderately above pre-treatment levels 30 minutes after esmolol hydrochloride discontinuation.

5.11 Use in Patients with Hyperthyroidism

Beta-adrenergic blockade may mask certain clinical signs (e.g., tachycardia) of hyperthyroidism. Abrupt withdrawal of beta-blockade might precipitate a thyroid storm; therefore, monitor patients for signs of thyrotoxicosis when withdrawing beta-blocking therapy.

5.12 Use in Patients at Risk of Severe Acute Hypersensitivity Reactions

When using beta-blockers, patients at risk of anaphylactic reactions may be more reactive to allergen exposure (accidental, diagnostic, or therapeutic).

Patients using beta-blockers may be unresponsive to the usual doses of epinephrine used to treat anaphylactic or anaphylactoid reactions [see Drug Interactions (7)].

6 ADVERSE REACTIONS

6.1 Clinical Trials Experience

Because clinical trials are conducted under widely varying conditions, adverse reaction rates observed in the clinical trials of a drug cannot be directly compared to rates in the clinical trials of another drug and may not reflect the rates observed in clinical practice.

The following adverse reaction rates are based on use of esmolol hydrochloride in clinical trials involving 369 patients with supraventricular tachycardia and over 600 intraoperative and postoperative patients enrolled in clinical trials. Most adverse effects observed in controlled clinical trial settings have been mild and transient. The most important and common adverse effect has been hypotension [see Warnings and Precautions (5.3)]. Deaths have been reported in post-marketing experience occurring during complex clinical states where esmolol hydrochloride was presumably being used simply to control ventricular rate [see Warnings and Precautions (5.5)].

Table 3. Clinical Trial Adverse Reactions (Frequency ≥3%)
(Frequency ≥3%) System Organ Class (SOC) | Preferred MedDRA Term | Frequency
Vascular Disorders | Hypotension* Asymptomatic hypotension Symptomatic hypotension (hyperhidrosis, dizziness) | 25%; 12%
General Disorders and Administration Site Conditions | Infusion site reactions (inflammation and induration) | 8%
Gastrointestinal Disorders | Nausea | 7%
Nervous System Disorders | Dizziness | 3%
Nervous System Disorders | Somnolence | 3%
* Hypotension resolved during Esmolol Hydrochloride infusion in 63% of patients. In 80% of the remaining patients, hypotension resolved within 30 minutes following discontinuation of infusion.

Clinical Trial Adverse Reactions (Frequency <3%)

Psychiatric Disorders

Confusional state and agitation (~2%)

Anxiety, depression and abnormal thinking (<1%)

Nervous System Disorders

Headache (~ 2%)

Paresthesia, syncope, speech disorder, and lightheadedness (<1%)

Convulsions (<1%), with one death

Vascular Disorders

Peripheral ischemia (~1%)

Pallor and flushing (<1%)

Gastrointestinal Disorders

Vomiting (~1%)

Dyspepsia, constipation, dry mouth, and abdominal discomfort have (<1%)

Renal and Urinary Disorders

Urinary retention (<1%)

6.2 Post-Marketing Experience

In addition to the adverse reactions reported in clinical trials, the following adverse reactions have been reported in the post-marketing experience. Because these reactions are reported voluntarily from a population of uncertain size, it is not always possible to estimate reliably their frequency or to establish a causal relationship to drug exposure.

Cardiac Disorders

Cardiac arrest, Coronary arteriospasm

Skin and Subcutaneous Tissue Disorders

Angioedema, Urticaria, Psoriasis

7 DRUG INTERACTIONS

Concomitant use of esmolol hydrochloride with other drugs that can lower blood pressure, reduce myocardial contractility, or interfere with sinus node function or electrical impulse propagation in the myocardium can exaggerate esmolol hydrochloride’s effects on blood pressure, contractility, and impulse propagation. Severe interactions with such drugs can result in, for example, severe hypotension, cardiac failure, severe bradycardia, sinus pause, sinoatrial block, atrioventricular block, and/or cardiac arrest.

1. Digitalis glycosides: Concomitant administration of digoxin and esmolol hydrochloride leads to an approximate 10% to 20% increase of digoxin blood levels at some time points. Digoxin does not affect esmolol hydrochloride pharmacokinetics. Both digoxin and beta-blockers slow atrioventricular conduction and decrease heart rate. Concomitant use increases the risk of bradycardia.
2. Anticholinesterases: Esmolol hydrochloride prolonged the duration of succinylcholine-induced neuromuscular blockade and moderately prolonged clinical duration and recovery index of mivacurium.
3. Antihypertensive agents clonidine or guanfacine: Beta-blockers also increase the risk of clonidine-, or guanfacine-withdrawal rebound hypertension. If, during concomitant use of a beta-blocker, antihypertensive therapy needs to be interrupted or discontinued, discontinue the beta-blocker first, and the discontinuation should be gradual.
4. Calcium channel antagonists: In patients with depressed myocardial function, use of esmolol hydrochloride with cardiodepressant calcium channel antagonists (e.g., verapamil) can lead to fatal cardiac arrests.
5. Sympathomimetic drugs: Sympathomimetic drugs having beta-adrenergic agonist activity will counteract effects of esmolol hydrochloride.
6. Vasoconstrictive and positive inotropic agents: Because of the risk of reducing cardiac contractility in presence of high systemic vascular resistance, do not use esmolol hydrochloride to control tachycardia in patients receiving drugs that are vasoconstrictive and have positive inotropic effects, such as epinephrine, norepinephrine, and dopamine.

8 USE IN SPECIFIC POPULATIONS

8.1 Pregnancy

Risk Summary

Available data from published case reports, case series and clinical studies over decades of use with Esmolol during pregnancy are insufficient to identify a drug-associated risk of major birth defects, miscarriage, or adverse maternal outcomes. Esmolol use in the last trimester of pregnancy or during labor or delivery has been reported to cause fetal bradycardia, which continued after termination of the drug infusion (see Clinical Considerations). In animal reproductive studies, administration of esmolol hydrochloride to pregnant rats during the period of organogenesis did not demonstrate embryotoxicity or teratogenicity at doses up to approximately 1.6 times the maximum human maintenance dose (300 mcg/kg/min). In rabbits, intravenous administration of esmolol hydrochloride at approximately 2.7 times the maximum human maintenance dose (300 mcg/kg/min) during organogenesis produced minimal maternal toxicity and increased fetal resorptions (see Data).

The background risk of major birth defects and miscarriage for the indicated population is unknown. In the U.S. general population, the estimated background risk of major birth defects and miscarriage in clinically recognized pregnancies is 2 to 4% and 15 to 20%, respectively.

Clinical Considerations

Fetal/Neonatal Adverse Reactions

Esmolol use in the last trimester of pregnancy or during labor or delivery has been reported to cause fetal bradycardia, which continued after termination of the drug infusion. Because of hypotension to the mother, monitor the pregnant woman for decreased uterine blood flow and resulting fetal hypoxia.

Data

Animal Data

In animal reproduction studies, administration of esmolol during organogenesis, in the rat study did not demonstrate embryotoxicity or teratogenicity in doses up to 3,000 mcg (3 mg)/kg/min for 30 min. Based on body surface area, this dose is approximately 1.6 times the maximum human maintenance dose (300 mcg/kg/min). In rabbits, intravenous dosage of 2,500 mcg (2.5 mg)/kg/min during organogenesis, produced minimal maternal toxicity and increased fetal resorptions, which is approximately 2.7 times the maximum human maintenance dose (300 mcg/kg/min).

8.2 Lactation

Risk Summary

There are no data on the presence of esmolol or its metabolite in either human or animal milk, the effects of the drug on the breastfed infant, or the effects of the drug on milk production. Consider the developmental and health benefits of breastfeeding along with the mother’s clinical need for esmolol and any potential adverse effects on the breastfed infant from esmolol hydrochloride or from the underlying maternal condition.

8.4 Pediatric Use

The safety and effectiveness of esmolol hydrochloride in pediatric patients have not been established.

8.5 Geriatric Use

Clinical studies of esmolol hydrochloride did not include sufficient numbers of subjects aged 65 and over to determine whether they responded differently from younger subjects. Other reported clinical experience has not identified differences in responses between the elderly and younger patients. In general, dose selection for an elderly patient should usually start at the low end of the dosing range, reflecting greater frequency of decreased renal or cardiac function and of concomitant disease or other drug therapy.

8.6 Hepatic Impairment

No special precautions are necessary in patients with hepatic impairment because esmolol hydrochloride is metabolized by red-blood cell esterases [see Clinical Pharmacology (12.3)].

8.7 Renal Impairment

No dosage adjustment is required for esmolol in patients with renal impairment receiving a maintenance infusion of esmolol 150 mcg/kg for 4 hours. There is no information on the tolerability of maintenance infusions of esmolol using rates in excess of 150 mcg/kg or maintained longer than 4 hours [see Clinical Pharmacology (12.3)].

10 OVERDOSAGE

10.1 Signs and Symptoms of Overdose

Overdoses of esmolol hydrochloride can cause cardiac and central nervous system effects. These effects may precipitate severe signs, symptoms, sequelae, and complications (for example, severe cardiac and respiratory failure, including shock and coma), and may be fatal. Continuous monitoring of the patient is required.

- Cardiac effects include bradycardia, atrioventricular block (1st -, 2nd -, 3rd degree), junctional rhythms, intraventricular conduction delays, decreased cardiac contractility, hypotension, cardiac failure (including cardiogenic shock), cardiac arrest/asystole, and pulseless electrical activity.
- Central nervous system effects include respiratory depression, seizures, sleep and mood disturbances, fatigue, lethargy, and coma.
- In addition, bronchospasm, mesenteric ischemia, peripheral cyanosis, hyperkalemia, and hypoglycemia (especially in children) may occur.

10.2 Treatment Recommendations

Because of its approximately 9-minute elimination half-life, the first step in the management of toxicity should be to discontinue the esmolol hydrochloride infusion. Then, based on the observed clinical effects, consider the following general measures.

Bradycardia

Consider intravenous administration of atropine or another anticholinergic drug or cardiac pacing.

Cardiac Failure

Consider intravenous administration of a diuretic or digitalis glycoside. In shock resulting from inadequate cardiac contractility, consider intravenous administration of dopamine, dobutamine, isoproterenol, or inamrinone. Glucagon has been reported to be useful.

Symptomatic hypotension

Consider intravenous administration of fluids or vasopressor agents such as dopamine or norepinephrine.

Bronchospasm

Consider intravenous administration of a beta2 stimulating agent or a theophylline derivative.

11 DESCRIPTION

Esmolol Hydrochloride is a beta-adrenergic receptor blocker with a very short duration of action (elimination half-life is approximately 9 minutes). Esmolol hydrochloride is:

- (±)-Methyl p-[2-hydroxy-3-(isopropylamino) propoxy] hydrocinnamate hydrochloride and has the following structure:

- Esmolol hydrochloride has the empirical formula C16H26NO4Cl and a molecular weight of 331.8. It has one asymmetric center and exists as an enantiomeric pair.
- Esmolol hydrochloride is a white to off-white crystalline powder. It is a relatively hydrophilic compound which is very soluble in water and freely soluble in alcohol. Its partition coefficient (octanol/water) at pH 7.0 is 0.42 compared to 17.0 for propranolol.

Esmolol Hydrochloride is a clear, colorless to light yellow, sterile, non-pyrogenic solution of esmolol hydrochloride.

The formulations for Esmolol Hydrochloride are described in the table below:

Table 4. Esmolol Hydrochloride Formulations
 | Esmolol Hydrochloride | Esmolol Hydrochloride DOUBLE STRENGTH
Esmolol Hydrochloride | 10 mg/mL | 20 mg/mL
Ethanol | 1% v/v | 1% v/v
Propylene Glycol | 10 mg/mL | 10 mg/mL
Water for Injection, USP | Q.S. to volume of 250 mL | Q.S. to volume of 100 mL
Sodium Acetate Trihydrate , USP | 0.68 mg/mL | 0.68 mg/mL
Glacial Acetic Acid, USP | 0.27 mg/mL | 0.27 mg/mL
Osmolarity | 320 to 450 mOsmol/L | 440 to 500 mOsmol/L
Sodium Hydroxide | Q.S. to adjust pH to 5.0 (4.5 to 6.5)
Q.S. = Quantity sufficient

The 250 mL and 100 mL dual port bags have an aluminum overwrap and the container closure is not made with natural rubber latex.

Solutions in contact with the plastic container leach out certain chemical compounds from the plastic in very small amounts; however, biological testing was supportive of the safety of the plastic container materials.

12 CLINICAL PHARMACOLOGY

12.1 Mechanism of Action

Esmolol hydrochloride is a beta1-selective (cardioselective) adrenergic receptor blocking agent with rapid onset, a very short duration of action, and no significant intrinsic sympathomimetic or membrane stabilizing activity at therapeutic dosages. Its elimination half-life after intravenous infusion is approximately 9 minutes. Esmolol hydrochloride inhibits the beta1 receptors located chiefly in cardiac muscle, but this preferential effect is not absolute and at higher doses it begins to inhibit beta2 receptors located chiefly in the bronchial and vascular musculature.

12.2 Pharmacodynamics

Clinical pharmacology studies in normal volunteers have confirmed the beta-blocking activity of esmolol hydrochloride showing reduction in heart rate at rest and during exercise, and attenuation of isoproterenol-induced increases in heart rate. Blood levels of esmolol hydrochloride have been shown to correlate with extent of beta-blockade. After termination of infusion, substantial recovery from beta-blockade is observed in 10 to 20 minutes. The acid metabolite of esmolol exhibits negligible pharmacological activity.

In human electrophysiology studies, esmolol hydrochloride produced effects typical of a beta-blocker; a decrease in heart rate, increase in sinus cycle length, prolongation of the sinus node recovery time, prolongation of the AH interval during normal sinus rhythm and during atrial pacing, and an increase in antegrade Wenckebach cycle length.

In patients undergoing radionuclide angiography, esmolol hydrochloride, at dosages of 200 mcg/kg/min, produced reductions in heart rate, systolic blood pressure, rate pressure product, left and right ventricular ejection fraction and cardiac index at rest, which were similar in magnitude to those produced by intravenous propranolol (4 mg). During exercise, esmolol hydrochloride produced reductions in heart rate, rate pressure product and cardiac index that were also similar to those produced by propranolol, but esmolol hydrochloride produced a significantly larger fall in systolic blood pressure. In patients undergoing cardiac catheterization, the maximum therapeutic dose of 300 mcg/kg/min of esmolol hydrochloride produced similar effects and, in addition, there were small, clinically insignificant increases in the left ventricular end diastolic pressure and pulmonary capillary wedge pressure. At 30 minutes after the discontinuation of esmolol hydrochloride infusion, all of the hemodynamic parameters had returned to pretreatment levels.

The relative cardioselectivity of esmolol hydrochloride was demonstrated in 10 mildly asthmatic patients. Infusions of esmolol hydrochloride 100, 200 and 300 mcg/kg/min produced no significant increases in specific airway resistance compared to placebo. At 300 mcg/kg/min, esmolol hydrochloride produced slightly enhanced bronchomotor sensitivity to dry air stimulus. These effects were not clinically significant, and esmolol hydrochloride was well tolerated by all patients. Six of the patients also received intravenous propranolol, and at a dosage of 1 mg, two experienced significant, symptomatic bronchospasm requiring bronchodilator treatment. One other propranolol-treated patient also experienced dry air-induced bronchospasm. No adverse pulmonary effects were observed in patients with COPD who received therapeutic dosages of esmolol hydrochloride for treatment of supraventricular tachycardia (51 patients) or in perioperative settings (32 patients).

12.3 Pharmacokinetics

Esmolol is rapidly metabolized by hydrolysis of the ester linkage, chiefly by the esterases in the cytosol of red blood cells and not by plasma cholinesterases or red cell membrane acetylcholinesterase. Total body clearance in man was found to be about 20 L/kg/hr, which is greater than cardiac output; thus the metabolism of esmolol is not limited by the rate of blood flow to metabolizing tissues such as the liver or affected by hepatic or renal blood flow. Esmolol has a rapid distribution half-life of about 2 minutes and an elimination half-life of about 9 minutes.

Using an appropriate loading dose, steady-state blood levels of esmolol hydrochloride for dosages from 50-300 mcg/kg/min are obtained within five minutes. Steady-state is reached in about 30 minutes without the loading dose. Steady-state blood levels of esmolol increase linearly over this dosage range and elimination kinetics are dose-independent over this range. Steady-state blood levels are maintained during infusion but decrease rapidly after termination of the infusion. Because of its short half-life, blood levels of esmolol can be rapidly altered by increasing or decreasing the infusion rate and rapidly eliminated by discontinuing the infusion.

Consistent with the high rate of blood-based metabolism of esmolol, less than 2% of the drug is excreted unchanged in the urine. Within 24 hours of the end of infusion, the acid metabolite of esmolol in urine accounts for approximately 73 to 88% of the dosage.

Metabolism of esmolol results in the formation of the corresponding free acid and methanol. The acid metabolite has been shown in animals to have negligible activity, and in normal volunteers its blood levels do not correspond to the level of beta-blockade. The acid metabolite has an elimination half-life of about 3.7 hours and is excreted in the urine with a clearance approximately equivalent to the glomerular filtration rate.

After a 4 hour maintenance infusion of 150 mcg/kg, the plasma concentrations of esmolol are similar in subjects with normal renal function and in patients with ESRD on dialysis. The half-life of the acid metabolite of esmolol hydrochloride, which is primarily excreted unchanged by the kidney, is increased about 12-fold to 48 hours in patients with ESRD. The peak concentrations of the acid metabolite are doubled in ESRD.

Methanol blood levels, monitored in subjects receiving esmolol hydrochloride for up to 6 hours at 300 mcg/kg/min and 24 hours at 150 mcg/kg/min, approximated endogenous levels and were less than 2% of levels usually associated with methanol toxicity.

Esmolol hydrochloride has been shown to be 55% bound to human plasma protein, while the acid metabolite is only 10% bound.

13 NONCLINICAL TOXICOLOGY

Mutagenicity studies were conducted with Esmolol Hydrochloride using the Ames Test. Mutagenicity was not observed with esmolol.

Because of its short term usage no carcinogenicity or reproductive performance studies have been conducted with esmolol.

14 CLINICAL STUDIES

Supraventricular Tachycardia

In two multicenter, randomized, double-blind, controlled comparisons of esmolol hydrochloride with placebo and propranolol, maintenance doses of 50 to 300 mcg/kg/min of esmolol hydrochloride were found to be more effective than placebo and about as effective as propranolol, 3 to 6 mg given by bolus injections, in the treatment of supraventricular tachycardia, principally atrial fibrillation and atrial flutter. The majority of these patients developed their arrhythmias postoperatively. About 60 to 70% of the patients treated with esmolol hydrochloride developed either a 20% reduction in heart rate, a decrease in heart rate to less than 100 bpm, or, rarely, conversion to normal sinus rhythm and about 95% of these patients did so at a dosage of 200 mcg/kg/min or less. The average effective dosage of esmolol hydrochloride was approximately 100 mcg/kg/min in the two studies. Other multicenter baseline-controlled studies gave similar results. In the comparison with propranolol, about 50% of patients in both the esmolol hydrochloride and propranolol groups were on concomitant digoxin. Response rates were slightly higher with both beta-blockers in the digoxin-treated patients.

In all studies, significant decreases of blood pressure occurred in 20 to 50% of patients, identified either as adverse reaction reports by investigators, or by observation of systolic pressure less than 90 mmHg or diastolic pressure less than 50 mmHg. The hypotension was symptomatic (mainly hyperhidrosis or dizziness) in about 12% of patients, and therapy was discontinued in about 11% of patients, about half of whom were symptomatic. Hypotension was more common with esmolol hydrochloride (53%) than with propranolol (17%). The hypotension was rapidly reversible with decreased infusion rate or after discontinuation of therapy with esmolol hydrochloride. For both esmolol hydrochloride and propranolol, hypotension was reported less frequently in patients receiving concomitant digoxin.

16 HOW SUPPLIED/STORAGE AND HANDLING

16.1 How Supplied

Esmolol Hydrochloride is a clear, colorless to light yellow, sterile, non-pyrogenic solution that is available in a single-dose 250 mL dual port bag with an aluminum overwrap. The container closure is not made with natural rubber latex. It is available in the following presentation:

Strength | Package | NDC Number
2500 mg; (10 mg/mL) | 10 bags per carton | 44567-811-10

Esmolol Hydrochloride DOUBLE STRENGTH is a clear, colorless to light yellow, sterile, non-pyrogenic solution that is available in a single-dose 100 mL dual port bag with an aluminum overwrap. The container closure is not made with natural rubber latex. It is available in the following presentation:

Strength | Package | NDC Number
2000 mg; (20 mg/mL) | 10 bags per carton | 44567-812-10

16.2 Storage

Store at 20° to 25°C (68° to 77°F); excursions are permitted from 15° to 30°C (59° to 86°F) [See USP Controlled Room Temperature]. PROTECT FROM FREEZING. Avoid excessive heat.

Do not remove unit from overwrap until ready to use. Do not use if overwrap has been previously opened or damaged. The overwrap is a moisture barrier. The inner bag maintains sterility of the solution. Tear overwrap at notch and remove premixed bag.

17 PATIENT COUNSELING INFORMATION

Inform patients of the risks associated with Esmolol Hydrochloride:

- The most common adverse reactions are symptomatic hypotension (hyperhidrosis, dizziness) and asymptomatic hypotension.
- Inform patients or caregivers that there is a risk of hypoglycemia when esmolol hydrochloride is given to patients who are fasting or who are vomiting. Instruct patients or caregivers how to monitor for signs of hypoglycemia [see Warnings and Precautions (5.5)].

Rx only

Manufactured for:

WG Critical Care, LLC

Paramus, NJ 07652

Made in Switzerland

U.S. Patent Numbers 8,829,054 and 8,835,505

PRINCIPAL DISPLAY PANEL - 2000 MG/100 ML

NDC 44567-812-10

Esmolol Hydrochloride in Water for Injection

2000 mg/100 mL

(20 mg/mL)

PRINCIPAL DISPLAY PANEL - 2500 MG/250 ML

NDC 44567-811-10

Esmolol Hydrochloride in Water for Injection

2500 mg/250 mL

(10 mg/mL)